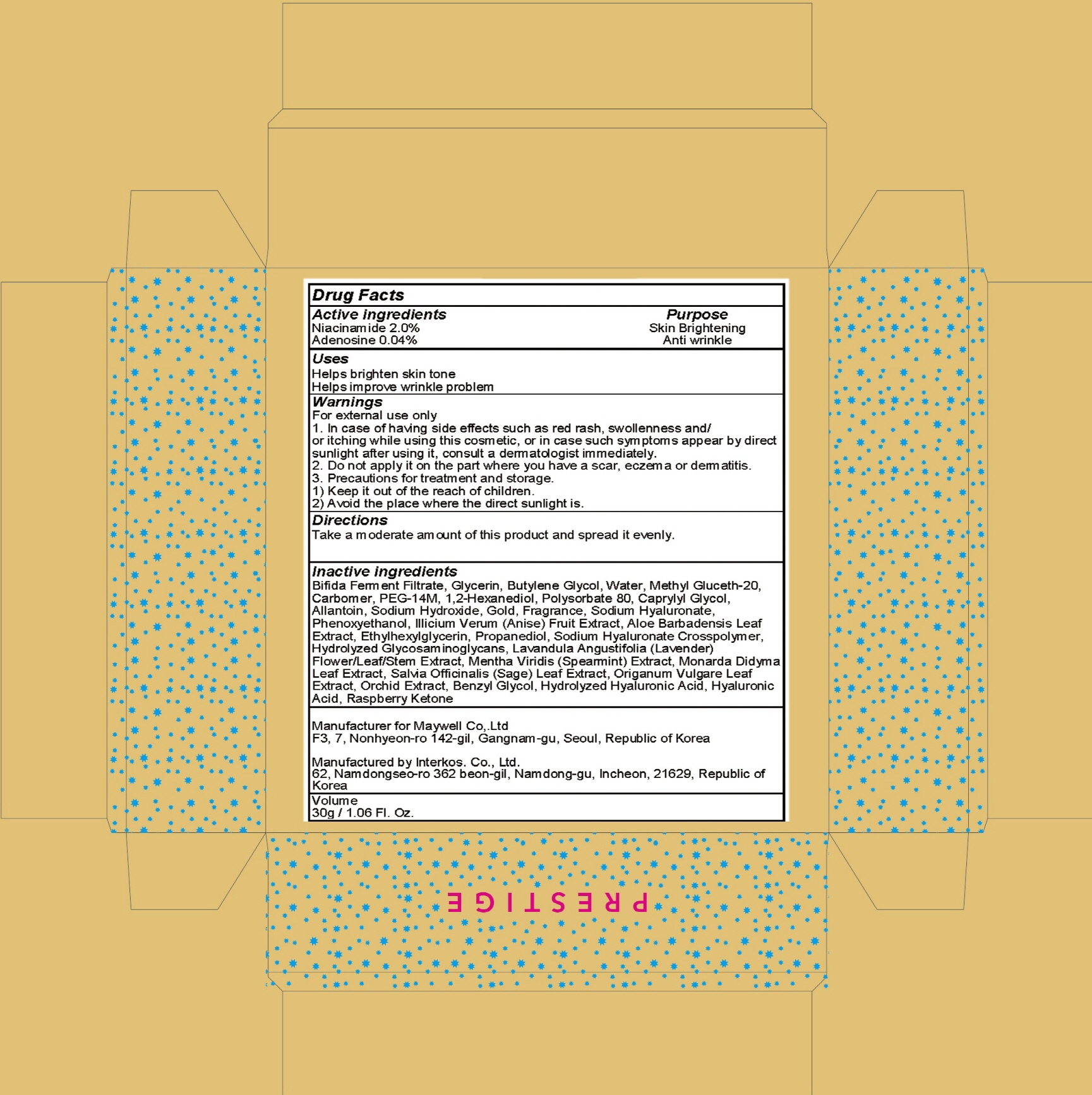 DRUG LABEL: Prestige Shiny Gold
NDC: 69628-020 | Form: CREAM
Manufacturer: Maywell Co,. Ltd.
Category: otc | Type: HUMAN OTC DRUG LABEL
Date: 20180919

ACTIVE INGREDIENTS: Niacinamide 0.60 g/30 g; Adenosine 0.01 g/30 g
INACTIVE INGREDIENTS: Glycerin; Butylene Glycol

ACTIVE INGREDIENT

Active ingredients: Niacinamide 2.0%, Adenosine 0.04%

INACTIVE INGREDIENT

Inactive ingredients:

Bifida Ferment Filtrate, Glycerin, Butylene Glycol, Water, Methyl Gluceth-20, Carbomer, PEG-14M, 1,2-Hexanediol, Polysorbate 80, Caprylyl Glycol, Allantoin, Sodium Hydroxide, Gold, Fragrance, Sodium Hyaluronate, Phenoxyethanol, Illicium Verum (Anise) Fruit Extract, Aloe Barbadensis Leaf Extract, Ethylhexylglycerin, Propanediol, Sodium Hyaluronate Crosspolymer, Hydrolyzed Glycosaminoglycans, Lavandula Angustifolia (Lavender) Flower/Leaf/Stem Extract, Mentha Viridis (Spearmint) Extract, Monarda Didyma Leaf Extract, Salvia Officinalis (Sage) Leaf Extract, Origanum Vulgare Leaf Extract, Orchid Extract, Benzyl Glycol, Hydrolyzed Hyaluronic Acid, Hyaluronic Acid, Raspberry Ketone

PURPOSE

Purpose: Skin Brightening, Anti wrinkle

WARNINGS

For external use only

1. In case of having side effects such as red rash, swollenness and/or itching while using this cosmetic, or in case such symptoms appear by direct sunlight after using it, consult a dermatologist immediately.

2. Do not apply it on the part where you have a scar, eczema or dermatitis.

3. Precautions for treatment and storage.

1) Keep it out of the reach of children.

2) Avoid the place where the direct sunlight is.

KEEP OUT OF REACH OF CHILDREN

Keep it out of the reach of children.

Uses

Helps brighten skin tone

Helps improve wrinkle problem

Directions

Take a moderate amount of this product and spread it evenly.